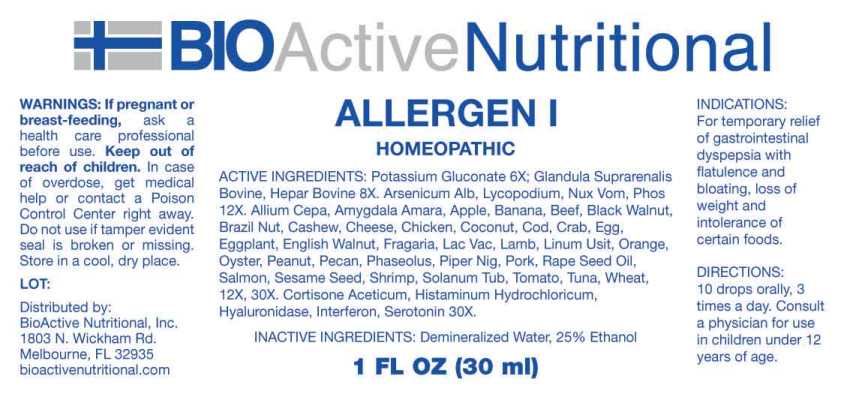 DRUG LABEL: Allergen
NDC: 43857-0626 | Form: LIQUID
Manufacturer: BioActive Nutritional
Category: homeopathic | Type: HUMAN OTC DRUG LABEL
Date: 20241002

ACTIVE INGREDIENTS: POTASSIUM GLUCONATE 6 [hp_X]/1 mL; BOS TAURUS ADRENAL GLAND 8 [hp_X]/1 mL; HEPARIN, BOVINE 8 [hp_X]/1 mL; ARSENIC TRIOXIDE 12 [hp_X]/1 mL; LYCOPODIUM CLAVATUM SPORE 12 [hp_X]/1 mL; STRYCHNOS NUX-VOMICA SEED 12 [hp_X]/1 mL; PHOSPHORUS 12 [hp_X]/1 mL; PEANUT 12 [hp_X]/1 mL; BLACK WALNUT 12 [hp_X]/1 mL; ENGLISH WALNUT 12 [hp_X]/1 mL; BITTER ALMOND 12 [hp_X]/1 mL; CASHEW 12 [hp_X]/1 mL; COCONUT 12 [hp_X]/1 mL; PECAN 12 [hp_X]/1 mL; BRAZIL NUT 12 [hp_X]/1 mL; TOMATO 12 [hp_X]/1 mL; SOLANUM TUBEROSUM WHOLE 12 [hp_X]/1 mL; GREEN PEPPERCORN 12 [hp_X]/1 mL; EGGPLANT 12 [hp_X]/1 mL; CANOLA OIL 12 [hp_X]/1 mL; FLAX SEED 12 [hp_X]/1 mL; SESAME SEED 12 [hp_X]/1 mL; CASEIN, LACTOCOCCUS LACTIS CULTURED, PENICILLIUM ROQUEFORTI CULTURED, AGED 12 [hp_X]/1 mL; COW MILK 12 [hp_X]/1 mL; BEEF 12 [hp_X]/1 mL; LAMB 12 [hp_X]/1 mL; PORK 12 [hp_X]/1 mL; CHICKEN 12 [hp_X]/1 mL; EGG 12 [hp_X]/1 mL; KIDNEY BEAN 12 [hp_X]/1 mL; ONION 12 [hp_X]/1 mL; APPLE 12 [hp_X]/1 mL; WHEAT 12 [hp_X]/1 mL; BANANA 12 [hp_X]/1 mL; FRAGARIA VESCA FRUIT 12 [hp_X]/1 mL; ORANGE 12 [hp_X]/1 mL; ATLANTIC COD 12 [hp_X]/1 mL; NORTHERN BLUEFIN TUNA 12 [hp_X]/1 mL; ATLANTIC SALMON 12 [hp_X]/1 mL; EDIBLE ROCK CRAB 12 [hp_X]/1 mL; PACIFIC OYSTER 12 [hp_X]/1 mL; CRANGON SHRIMP 12 [hp_X]/1 mL; CORTISONE ACETATE 30 [hp_X]/1 mL; HISTAMINE DIHYDROCHLORIDE 30 [hp_X]/1 mL; HYALURONIDASE (BOVINE) 30 [hp_X]/1 mL; INTERLEUKIN-1 .BETA. HUMAN 30 [hp_X]/1 mL; SEROTONIN HYDROCHLORIDE 30 [hp_X]/1 mL
INACTIVE INGREDIENTS: WATER; ALCOHOL

DRUG FACTS:

ACTIVE INGREDIENTS:

Potassium Gluconate 6X, Glandula Suprarenalis Bovine 8X, Hepar Bovine 8X, Arsenicum Album 12X, Lycopodium Clavatum 12X, Nux Vomica 12X, Phosphorus 12X, Peanut 12X, 30X, Black Walnut 12X, 30X, English Walnut 12X, 30X, Amygdala Amara 12X, 30X, Cashew 12X, 30X, Coconut 12X, 30X, Pecan 12X, 30X, Brazil Nut 12X, 30X, Tomato 12X, 30X, Solanum Tuberosum 12X, 30X, Piper Nigrum 12X, 30X, Eggplant (Solanum Melongena) 12X, 30X, Rape Seed Oil 12X, 30X, Cheese (Stilton) 12X, 30X, Linum Usitatissimum 12X, 30X, Sesame Seed 12X, 30X, Lac Vaccinum 12X, 30X, Beef 12X, 30X, Lamb 12X, 30X, Pork 12X, 30X, Chicken 12X, 30X, Egg (Whole) 12X, 30X, Phaseolus 12X, 30X, Allium Cepa 12X, 30X, Apple 12X, 30X, Wheat 12X, 30X, Banana 12X, 30X, Fragaria Vesca 12X, 30X, Orange 12X, 30X, Cod (Gadus Morhua) 12X, 30X, Tuna (Thunnus Thynnus) 12X, 30X, Salmon (Salmo Salar) 12X, 30X, Crab (Cancer Pagurus) 12X, 30X, Oyster (Crassostrea Gigas) 12X, 30X, Shrimp (Crangon Crangon) 12X, 30X, Cortisone Aceticum 30X, Histaminum Hydrochloricum 30X, Hyaluronidase 30X, Interferon (Human) 30X, Serotonin (Hydrochloride) 30X.

INDICATIONS:

For temporary relief of gastrointestinal dyspepsia with flatulence and bloating, loss of weight and intolerance of certain foods.

WARNINGS:

If pregnant or breast-feeding, ask a health care professional before use.

Keep out of reach of children. In case of overdose, get medical help or contact a Poison Control Center right away.

Do not use if tamper evident seal is broken or missing.

Store in a cool, dry place.

Keep out of reach of children. In case of overdose, get medical help or contact a Poison Control Center right away.

DIRECTIONS:

10 drops orally, 3 times a day. Consult a physician for use in children under 12 years of age.

INDICATIONS:

For temporary relief of gastrointestinal dyspepsia with flatulence and bloating, loss of weight and intolerance of certain foods.

INACTIVE INGREDIENTS:

Demineralized Water, 25% Ethanol

QUESTIONS:

Distributed by:
BioActive Nutritional, Inc.
1803 N. Wickham Rd.
Melbourne, FL 32935
bioactivenutritional.com

PACKAGE LABEL DISPLAY:

BIOActive Nutritional

ALLERGEN I

HOMEOPATHIC

1 FL OZ (30 ml)